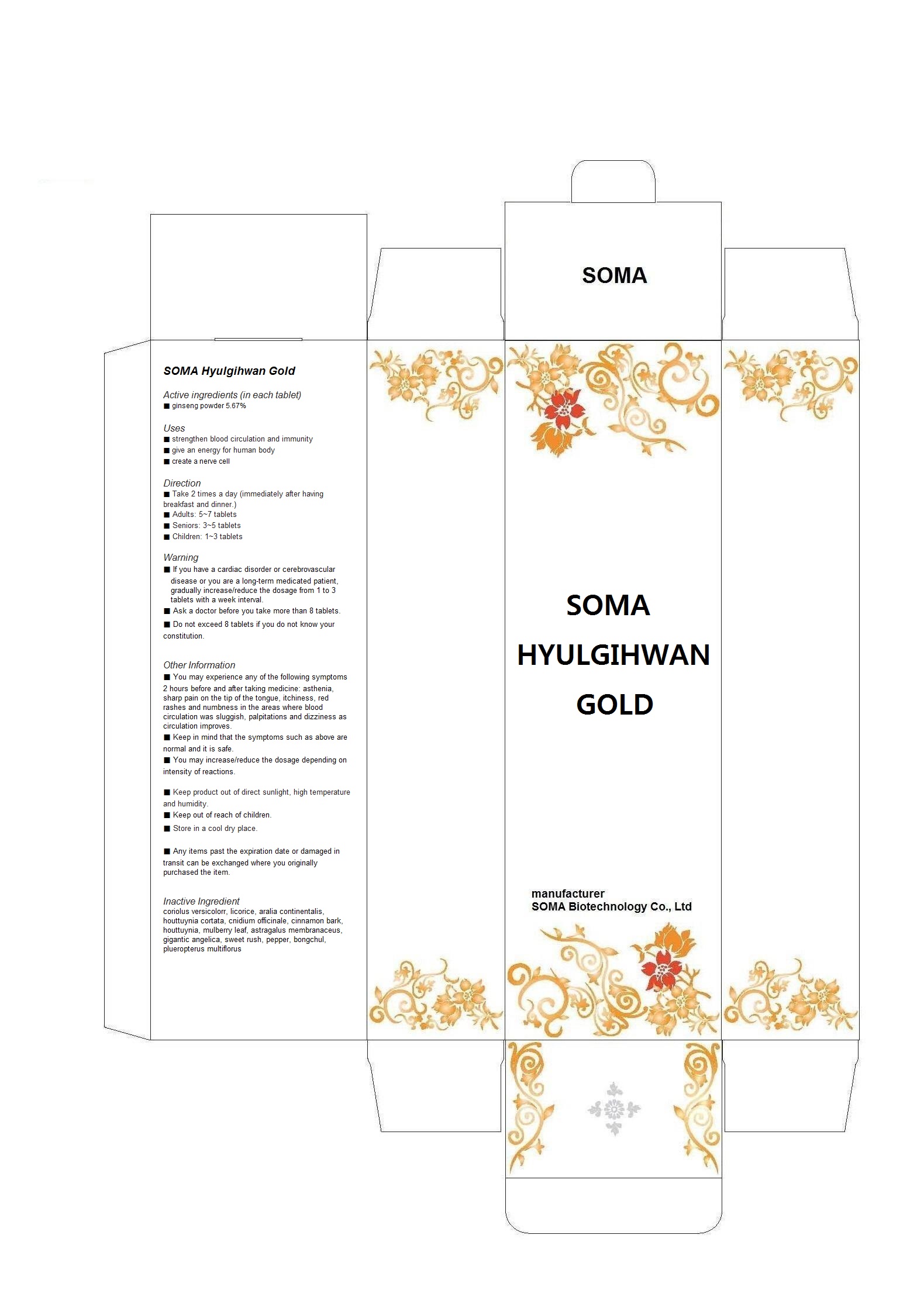 DRUG LABEL: SOMA Hyulgihwan Gold
NDC: 58370-1013 | Form: PILL
Manufacturer: SOMA Biotechnology Co., Ltd
Category: otc | Type: HUMAN OTC DRUG LABEL
Date: 20131114

ACTIVE INGREDIENTS: ASIAN GINSENG 0.0567 g/1 g
INACTIVE INGREDIENTS: CLOVE; GLYCYRRHIZA GLABRA; ARALIA CORDATA ROOT; HOUTTUYNIA CORDATA FLOWERING TOP; CNIDIUM OFFICINALE WHOLE; CINNAMON; MORUS AUSTRALIS LEAF; ASTRAGALUS PROPINQUUS ROOT; ANGELICA SINENSIS ROOT; ACORUS GRAMINEUS ROOT; PEPPERS; ZEDOARY; POLYGONUM CUSPIDATUM WHOLE; TRAMETES VERSICOLOR FRUITING BODY; CARAMEL

Drug Facts

ACTIVE INGREDIENT

ginseng powder

INACTIVE INGREDIENT

coriolus versicolorr, licorice, aralia continentalis, houttuynia cortata, cnidium officinale, cinnamon bark, houttuynia, mulberry leaf, astragalus membranaceus, gigantic angelica, sweet rush, pepper, bongchul, plueropterus multiflorus

PURPOSE

-strengthen blood circulation and immunity
-give an energy for human body
-create a nerve cell

keep out of reach of the children

INDICATIONS AND USAGE

- Take 2 times a day
- adults 5~7 pills
- seniors: 3~5 pills
- children: 1~3 pills

WARNINGS

If you have a cardiac disorder or cerebrovascular disease or you are a long-term medicated patient, gradually increase/reduce the dosage from 1 to 3 pills with a week interval.
- Ask a doctor before you take more than 8 pills.
- Do not exceed 8 pills if you do not know your constitution.

DOSAGE AND ADMINISTRATION

for oral use only